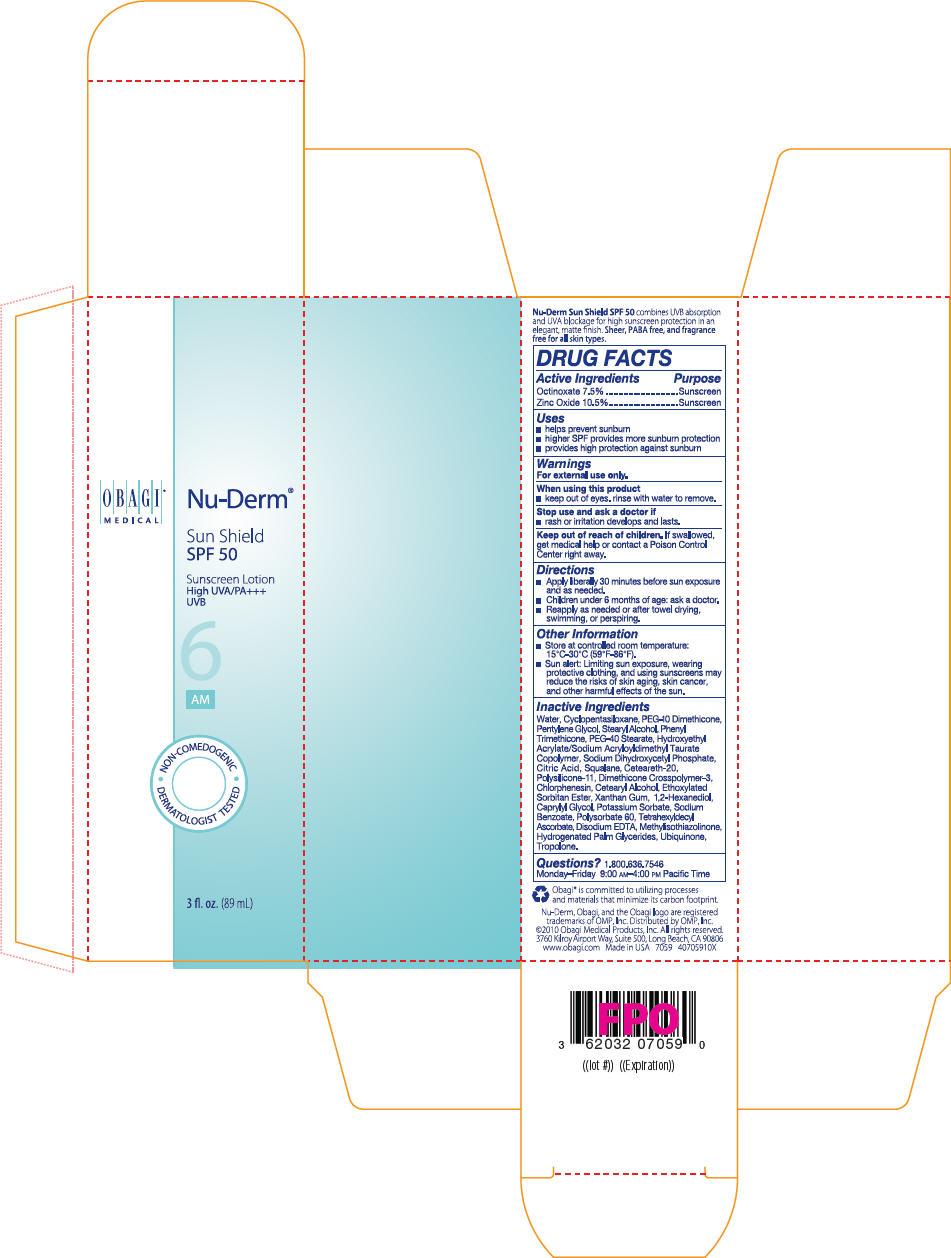 DRUG LABEL: NU-DERM SUN SHIELD SPF 50 SUNSCREEN
NDC: 62032-124 | Form: LOTION
Manufacturer: OMP, Inc.
Category: otc | Type: HUMAN OTC DRUG LABEL
Date: 20120110

ACTIVE INGREDIENTS: ZINC OXIDE 105 mg/1 mL; OCTINOXATE 75 mg/1 mL
INACTIVE INGREDIENTS: CYCLOMETHICONE 5; WATER; PEG-10 DIMETHICONE (600 CST); PENTYLENE GLYCOL; STEARYL ALCOHOL; POLYOXYL 20 CETOSTEARYL ETHER; PHENYL TRIMETHICONE; PEG-40 STEARATE; HYDROGENATED PALM GLYCERIDES; CITRIC ACID MONOHYDRATE; CETOSTEARYL ALCOHOL; 1,2-HEXANEDIOL; CAPRYLYL GLYCOL; TROPOLONE; CHLORPHENESIN; XANTHAN GUM; POTASSIUM SORBATE; SODIUM BENZOATE; TETRAHEXYLDECYL ASCORBATE; UBIDECARENONE; EDETATE DISODIUM; METHYLISOTHIAZOLINONE; SQUALANE; POLYSORBATE 60

NU-DERM®
SUN SHIELD
SPF 50

Drug Facts

ACTIVE INGREDIENT

Active Ingredients | Purpose
Octinoxate 7.5% | Sunscreen
Zinc Oxide 10.5% | Sunscreen

Uses

- helps prevent sunburn
- higher SPF provides more sunburn protection
- provides high protection against sunburn

Warnings

For external use only.

When using this product

- keep out of eyes. rinse with water to remove.

Stop use and ask a doctor if

- rash or irritation develops and lasts.

Keep out of reach of children. If swallowed, get medical help or contact a Poison Control Center right away.

Directions

- Apply liberally 30 minutes before sun exposure and as needed.
- Children under 6 months of age: ask a doctor.
- Reapply as needed or after towel drying, swimming, or perspiring.

Other Information

- Store at controlled room temperature:
  15°C-30° (59°F-86°F).
- Sun alert: Limiting sun exposure, wearing protective clothing, and using sunscreens may reduce the risks of skin aging, skin cancer, and other harmful effects of the sun.

Inactive Ingredients

Water, Cyclopentasiloxane, PEG-10 Dimethicone, Pentylene Glycol, Stearyl Alcohol, Phenyl Trimethicone, PEG-40 Stearate, Hydroxyethyl Acrylate/Sodium Acryloydimethyl Taurate Copolymer, Sodium Dihydroxycetyl Phosphate, Citric Acid, Squalane, Ceteareth-20, Polysilicone-11, Dimethicone Crosspolymer-3, Chlorphenesin, Cetearyl Alcohol, Ethoxylated Sorbitan Ester, Xanthan Gum, 1,2-Hexanediol, Caprylyl Glycol, Potassium Sorbate, Sodium Benzoate, Polysorbate 60, Tetrahexyldecyl Ascorbate, Disodium EDTA, Methylisothiazolinone, Hydrogenated Palm Glycerides, Ubiquinone, Tropolone.

Questions?

1.800.636.7546

Monday–Friday 9:00 AM–4:00 PM Pacific Time

Distributed by OMP, Inc.

PRINCIPAL DISPLAY PANEL - 89 mL Tube Carton

OBAGI®
MEDICAL

Nu-Derm®

Sun Shield
SPF 50

Sunscreen Lotion
High UVA/PA+++
UVB

6
AM

NON-COMEDOGENIC
DERMATOLOGIST TESTED

3 fl. oz. (89 mL)